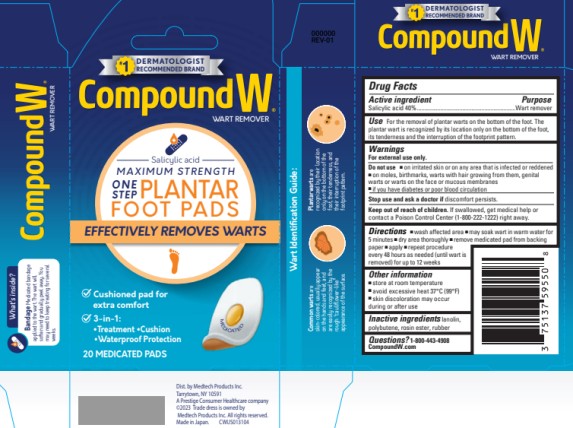 DRUG LABEL: Compound W One Step Plantar Foot Pads
NDC: 63029-593 | Form: PLASTER
Manufacturer: Medtech Products Inc.
Category: otc | Type: HUMAN OTC DRUG LABEL
Date: 20251023

ACTIVE INGREDIENTS: SALICYLIC ACID 0.4 g/1 1
INACTIVE INGREDIENTS: LANOLIN; POLYBUTENE (1400 MW); NATURAL LATEX RUBBER; GLYCERYL ROSINATE

Compound W One Step Plantar Foot Pads

Drug Facts

Active ingredient

Salicylic acid 40%

Purpose

Wart remover

Use

for the removal of plantar warts on the bottom of the foot. The plantar wart is recognized by its location only on the bottom of the foot, its tenderness and interruption of the footprint pattern.

Warnings

For external use only

Do not use

- on irritated skin or on any area that is infected or reddened.
- on moles, birthmarks, warts with hair growing from them, genital warts or warts on the face or mucous membranes
- if you have diabetes or poor blood circulation

Stop use and ask a doctor if

discomfort persists

Keep out of reach of children.

If swallowed, get medical help or contact a Poison Control Center (1-800-222-1222) right away.

Directions

- wash affected area
- may soak wart in warm water for 5 minutes
- dry area thoroughly
- remove medicated pad from backing paper by pulling from center of pad
- apply
- repeat procedure every 48 hours as needed (until wart is removed) for up to 12 weeks

Other information

- store at room temperature
- avoid excessive heat 37°C (99°F)
- skin discoloration may occur during or after use

Inactive ingredients

lanolin, polybutene, rosin ester, rubber

Questions?

1-800-443-4908 Compoundw.com

© 2023 Distributed by Medtech Products Inc.
Tarrytown NY 10591, a Prestige Brands Company
Made in Japan

PRINCIPAL DISPLAY PANEL

Compound W®
Salicylic Acid WART REMOVER
ONE STEP PLANTAR FOOT PADS
20 MEDICATED PADS